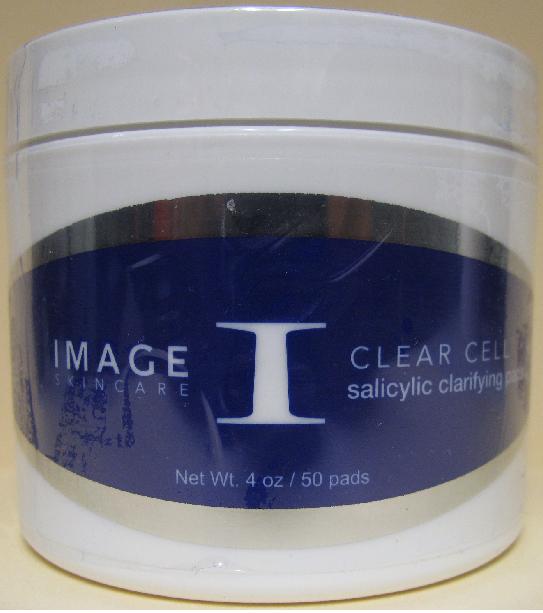 DRUG LABEL: Clear Cell Salicylic Clarifying Pads
NDC: 62742-4042 | Form: LIQUID
Manufacturer: Allure Labs, Inc.
Category: otc | Type: HUMAN OTC DRUG LABEL
Date: 20100721

ACTIVE INGREDIENTS: SALICYLIC ACID 50 mg/1 mL

Drug Facts

INDICATIONS AND USAGE SECTION:

A salicylic/glycolic acid skin pad to effectively remove impurities and excess oil. Deeply clears clogged pores and follicles to leave skin fresh and clean. A blend of anti-oxidants and calming ingredients reduce acneic inlfammation. Excellent for on the road cleaning and after physical activities.

Paraben Free

Effective home care exfoliation

DIRECTIONS:

Take out one pad at a time and apply by gently rubbing on entire face or affected areas. Use a broad spectrum sunscreen like the Sun solar defense oil free after usage.

ACTIVE INGREDIENT:

Salicylic Acid 5%

INACTIVE INGREDIENTS:

SD Alcohol 40-B(Alcohol Denat.), Water (Aqua), Glycerin, Glycolic Acid, PEG 8/SMDI Copolymer, Melaleuca Alternifolia (Tea Tree) Leaf Oil, Polysorbate 20, Allantoin, Aloe barbedensis Leaf Extract, Ammonium Hydroxide.

PACKAGE LABEL

DISTRIBUTOR:

IMAGE INTERNATIONAL

Palm Beach, FL 33411 USA

www.imageskincare.com